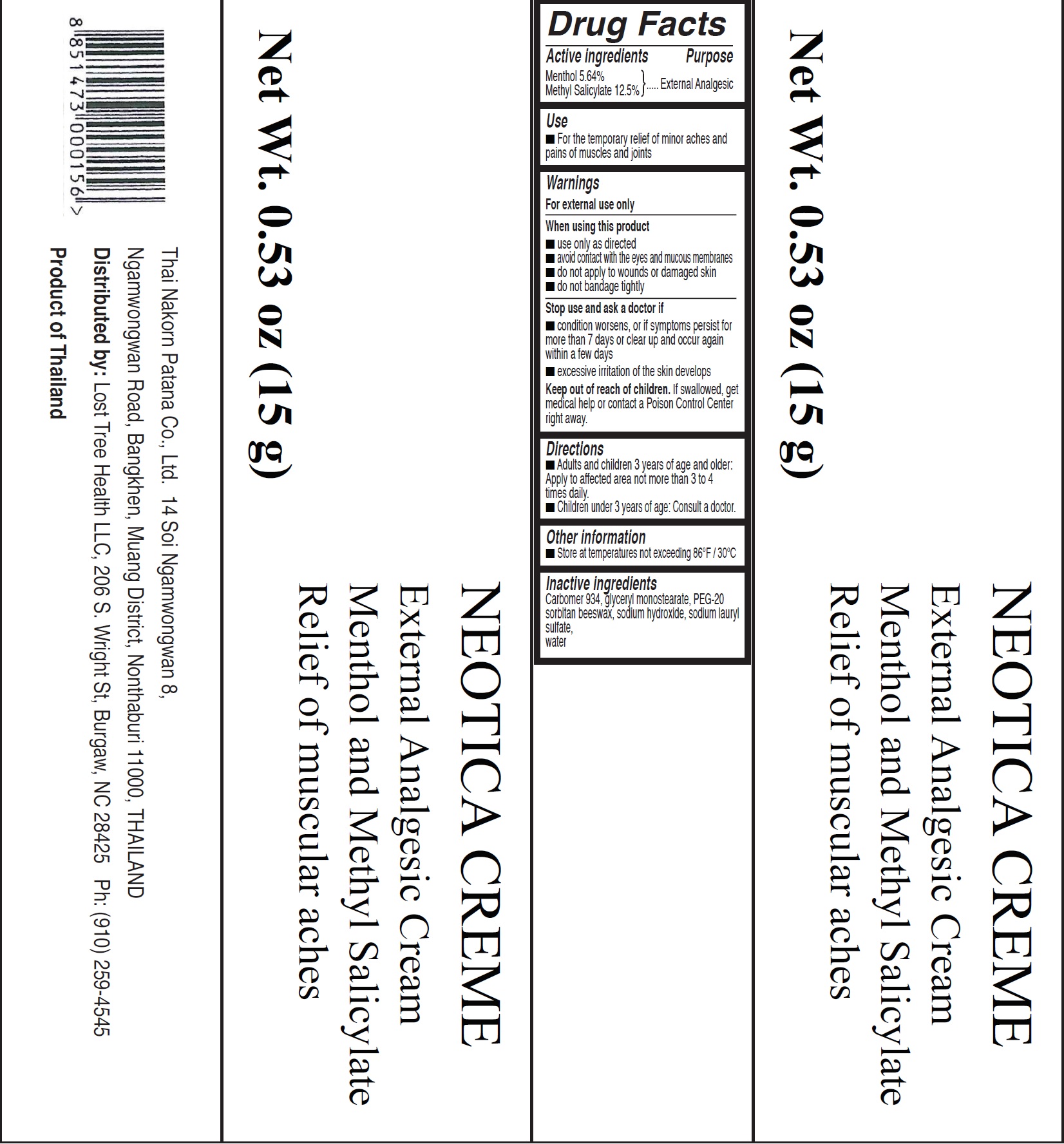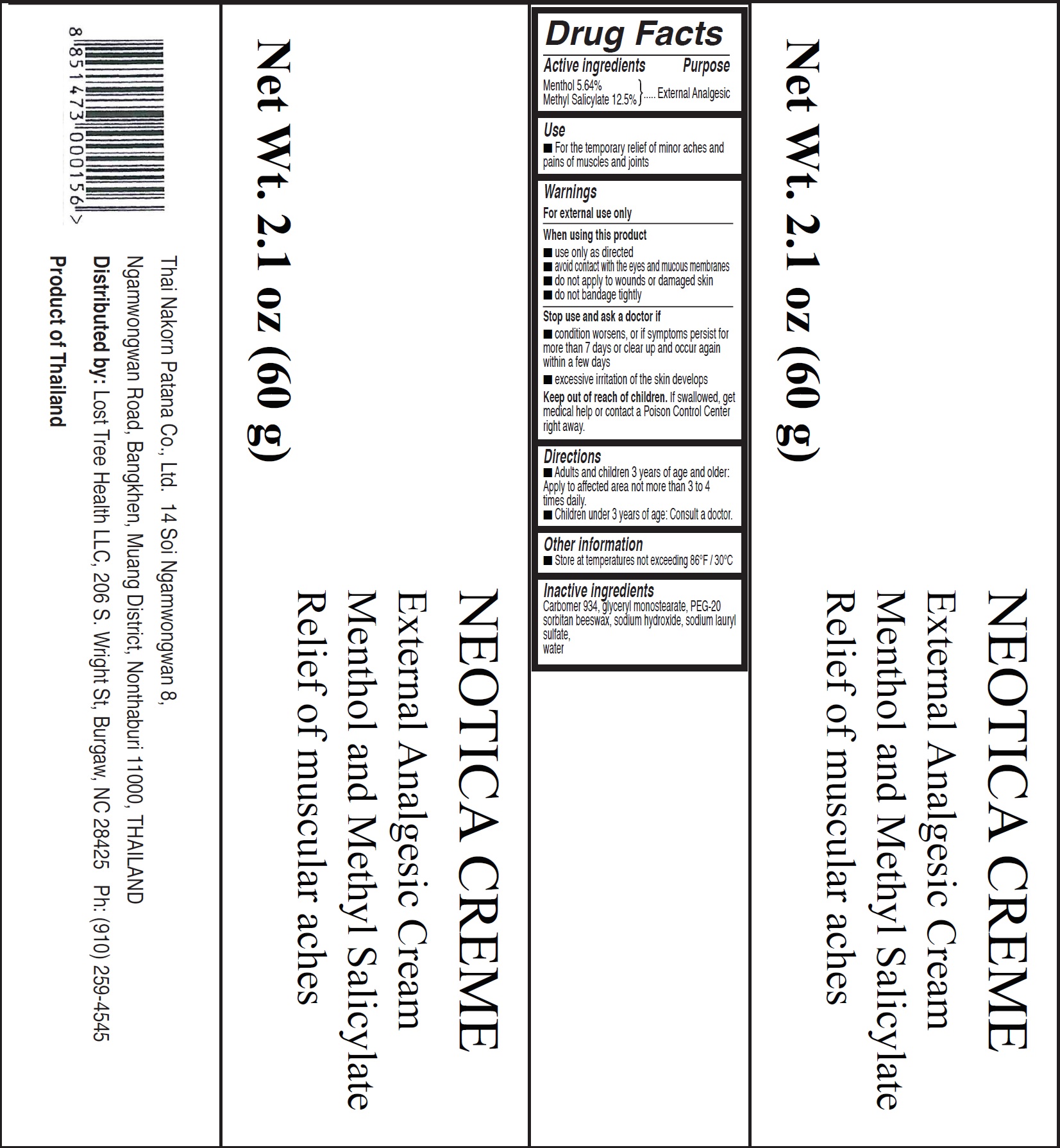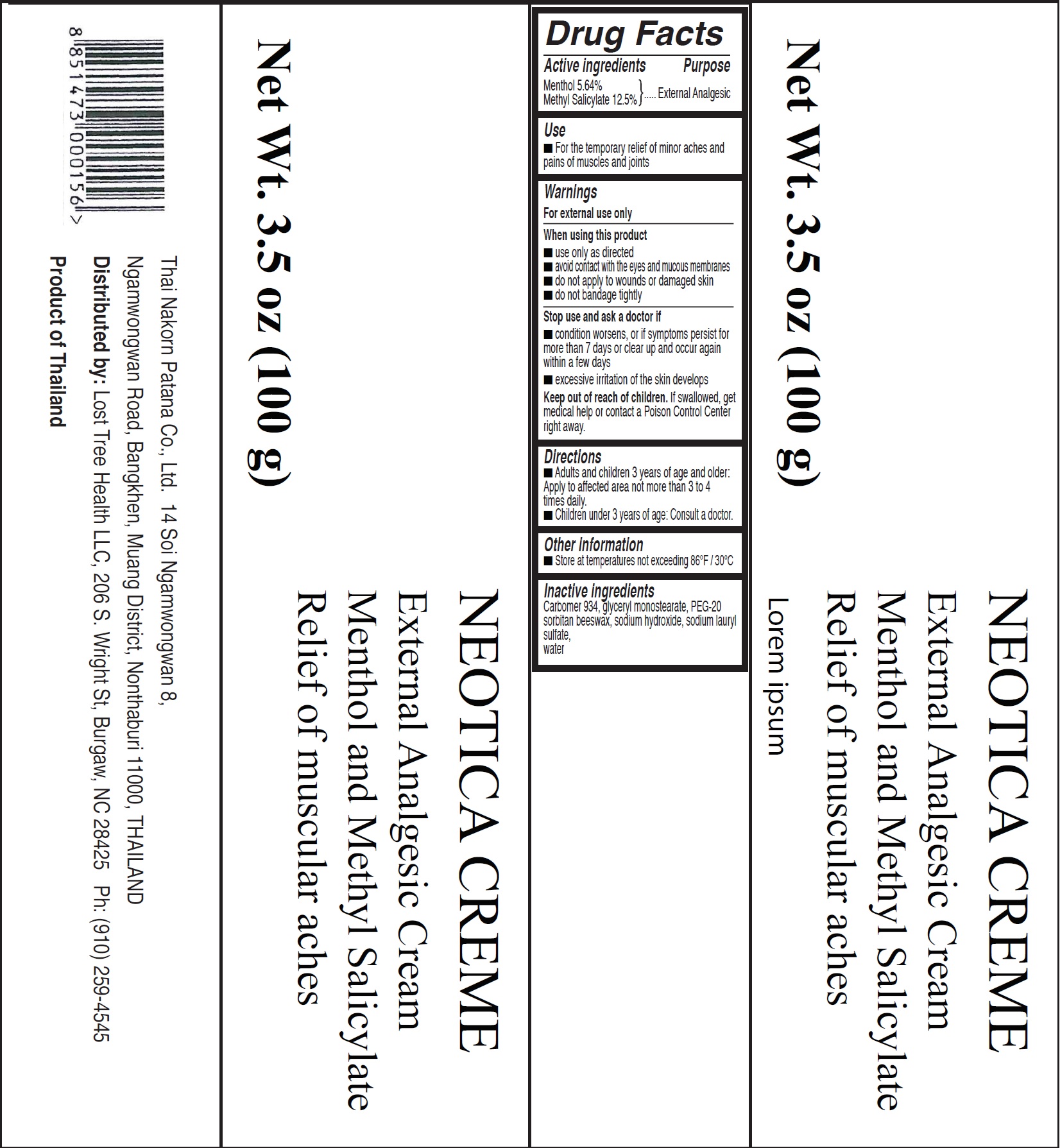 DRUG LABEL: Neotica
NDC: 72398-000 | Form: CREAM
Manufacturer: Lost Tree Health, LLC
Category: otc | Type: HUMAN OTC DRUG LABEL
Date: 20221025

ACTIVE INGREDIENTS: MENTHOL 56.4 mg/1 g; METHYL SALICYLATE 125 mg/1 g
INACTIVE INGREDIENTS: CARBOMER HOMOPOLYMER TYPE B (ALLYL SUCROSE CROSSLINKED); GLYCERYL MONOSTEARATE; SODIUM HYDROXIDE; SODIUM LAURYL SULFATE; WATER

Neotica Creme

Active ingredients

Menthol 5.64%

Methyl Salicylate 12.5%

Purpose

External Analgesic

Use

- For the temporary relief of minor aches and pains of muscles and joints

Warnings

For external use only

When using this product

- use only as directed
- avoid contact with the eyes and mucous membranes
- do not apply to wounds or damaged skin
- do not bandage tightly

Stop use and ask a doctor if

- condition worsens, or if symptoms persist for more than 7 days or clear up and occur again within a few days
- excessive irritation of the skin develops

Keep out of reach of children.

If swallowed, get medical help or contact a Poison Control Center right away.

Directions

- Adults and children 3 years of age and older: Apply to affected area not more than 3 to 4 times daily.
- Children under 3 years of age: Consult a doctor.

Other information

- Store at temperatures not exceeding 86°F / 30°C

Inactive ingredients

Carbomer 934, glyceryl monostearate, PEG-20 sorbitan beeswax, sodium hydroxide, sodium lauryl sulfate, water